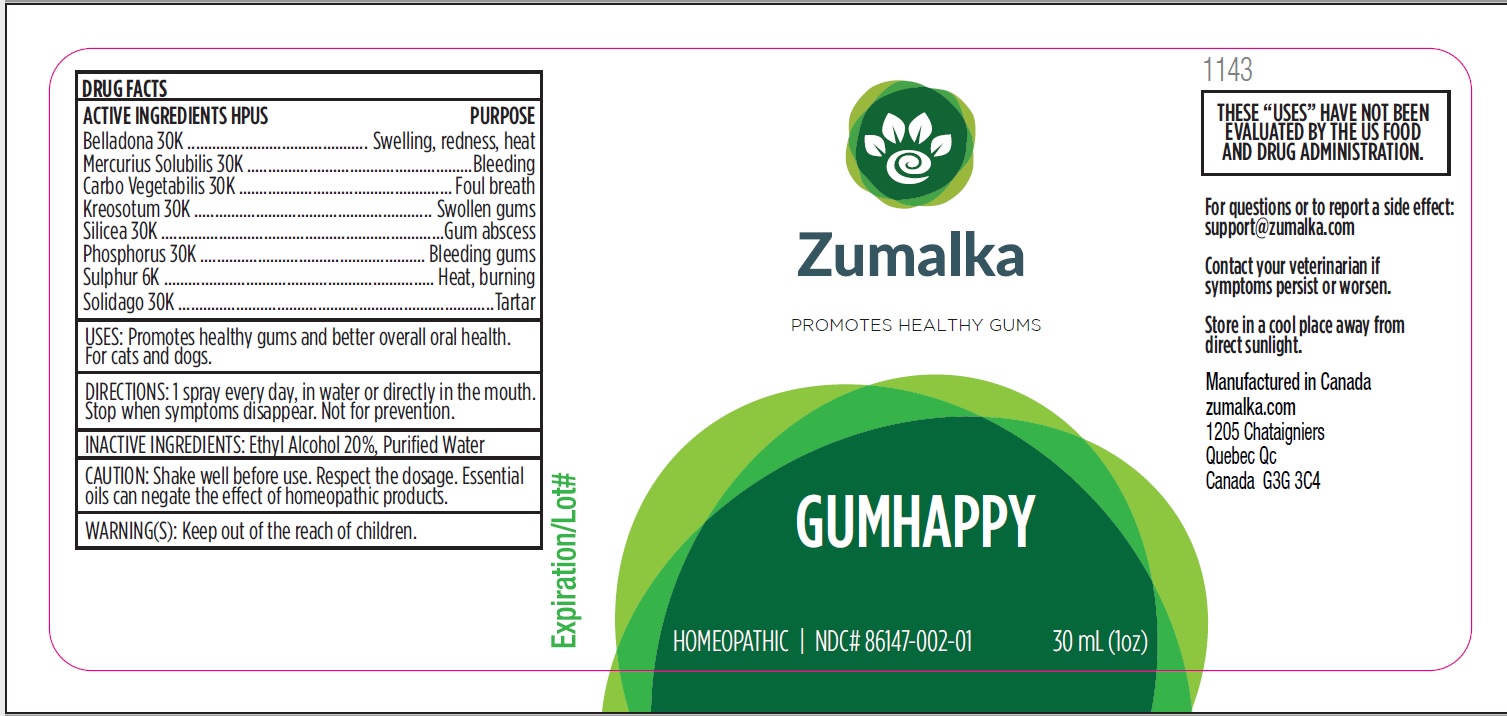 DRUG LABEL: GUMHAPPY
NDC: 86147-002 | Form: LIQUID
Manufacturer: Groupe Cyrenne Inc.
Category: homeopathic | Type: OTC ANIMAL DRUG LABEL
Date: 20251120

ACTIVE INGREDIENTS: ATROPA BELLADONNA 30 [kp_C]/30 mL; MERCURIUS SOLUBILIS 30 [kp_C]/30 mL; ACTIVATED CHARCOAL 30 [kp_C]/30 mL; PHOSPHORUS 30 [kp_C]/30 mL; SOLIDAGO VIRGAUREA FLOWERING TOP 30 [kp_C]/30 mL; WOOD CREOSOTE 30 [kp_C]/30 mL; SILICON DIOXIDE 30 [kp_C]/30 mL; SULFUR 6 [kp_C]/30 mL
INACTIVE INGREDIENTS: ALCOHOL; WATER

Active ingredient Purpose

Belladonna 30k Swelling, redness, heat

Mercurius Solubilis 30k Bleeding

Carbo Vegetabilis 30k Foul breath

Kreosotum 30k Swollen gums

Silicea 30k Gum abscess

Phosphorus 30k Bleeding gums

Sulphur 6k Heat, burning

Solidago 30k Tartar

Uses

Promotes healthy gums and better overall oral health. For cats and dogs only.

Warnings

Keep out of reach of children.

Direction

1 spray every day, in water or directly in the mouth. Stop when symptoms disappear. Not for prevention.

Inactive ingredient

Ethyl alcohol 20%, purified water

Cautions

Shake well before use. Respect the dosage. Essential oils can negate the effects of homeopathic products. Store in a cool place away from direct sunlight.